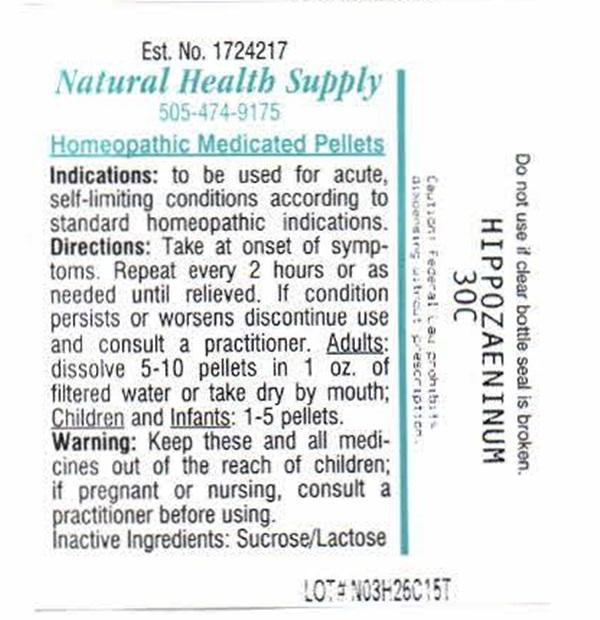 DRUG LABEL: HIPPOZAENINUM
NDC: 64117-404 | Form: PELLET
Manufacturer: Natural Health Supply
Category: homeopathic | Type: HUMAN PRESCRIPTION DRUG LABEL
Date: 20201203

ACTIVE INGREDIENTS: BURKHOLDERIA MALLEI 30 [hp_C]/1 1
INACTIVE INGREDIENTS: SUCROSE; LACTOSE

HIPPOZAENINUM 30C

Indications:

Indications: To be used for acute, self-limiting conditions according to standard homeopathic indications.

Directions:

Take at onset of symptoms. Repeat every 2 hours or as needed until relieved. If condition persists or worsens discontinue use and consult a practitioner.

Adults: dissolve 5 - 10 pellets in 1 oz. of filtered water or take dry by mouth;

Children and Infants: 1 - 5 pellets.

Warnings:

Keep these and all medications out of the reach of children; If prregnant or nursing, consult a practitioner before using.

Inactive Ingredients:

Sucrose/Lactose

Product Label Hippozaeninum

Est. No. 1724217

Natural Health Supply

505-474-9175

Homeopathic Medicated Pellets

Do not use if clear bottle seal is broken

HIPPOZAENINUM 30C

Caution: Federal Law prohibits dispensing without prescription

LOT # NO3H26C15T

res